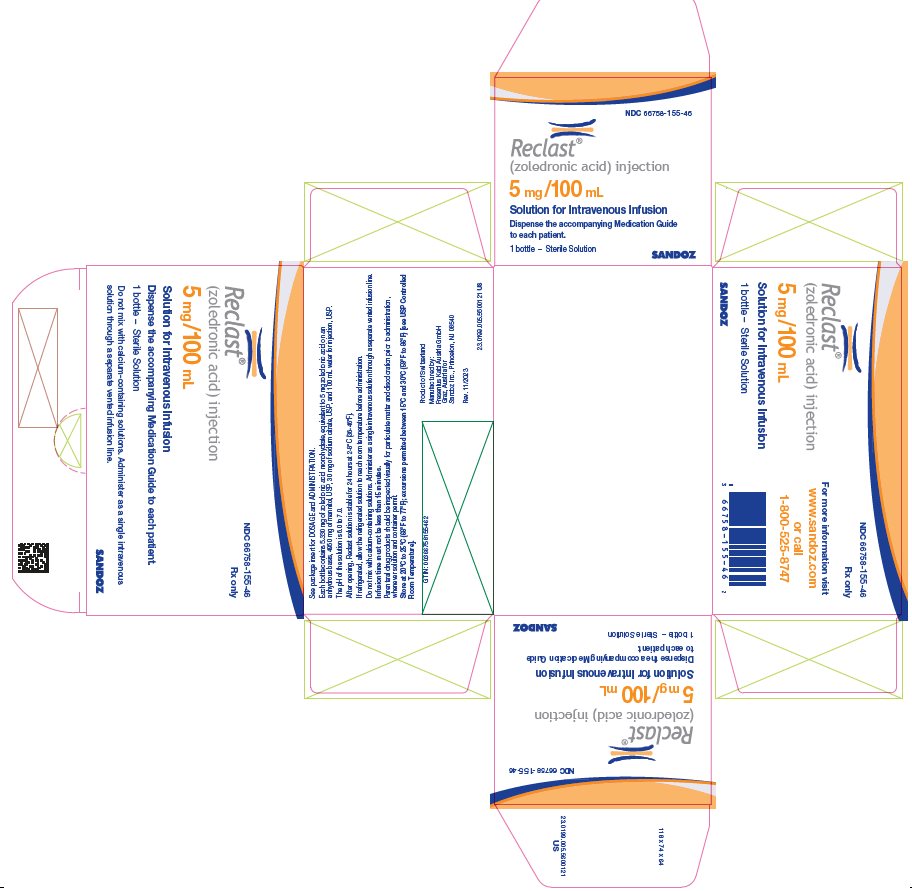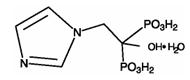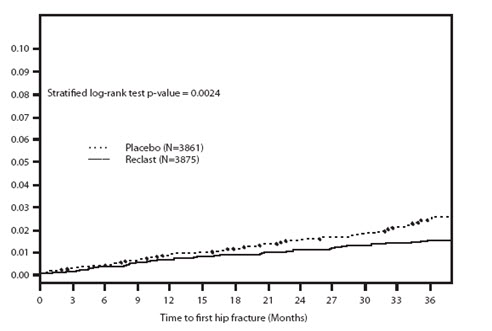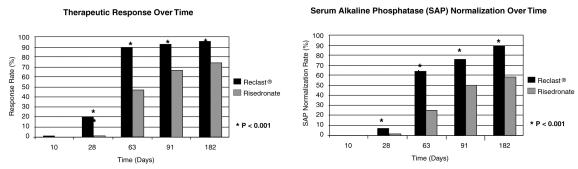 DRUG LABEL: Reclast
NDC: 66758-155 | Form: INJECTION, SOLUTION
Manufacturer: Sandoz Inc
Category: prescription | Type: HUMAN PRESCRIPTION DRUG LABEL
Date: 20260203

ACTIVE INGREDIENTS: ZOLEDRONIC ACID 5 mg/100 mL
INACTIVE INGREDIENTS: MANNITOL 4950 mg/100 mL; SODIUM CITRATE, UNSPECIFIED FORM 30 mg/100 mL; WATER

HIGHLIGHTS OF PRESCRIBING INFORMATION

These highlights do not include all the information needed to use RECLAST safely and effectively. See full prescribing information for RECLAST.
RECLAST® (zoledronic acid) Injection
Initial U.S. Approval: 2001

RECENT MAJOR CHANGES

Warnings and Precautions, Atypical Fractures Including Femoral Fractures (5.5) …………............................ 02/2026

1 INDICATIONS AND USAGE

Reclast is a bisphosphonate indicated for:

- Treatment and prevention of postmenopausal osteoporosis (1.1, 1.2)
- Treatment to increase bone mass in men with osteoporosis (1.3)
- Treatment and prevention of glucocorticoid-induced osteoporosis (1.4)
- Treatment of Paget’s disease of bone in men and women (1.5)

Limitations of Use

Optimal duration of use has not been determined. For patients at low-risk for fracture, consider drug discontinuation after 3 to 5 years of use (1.6)

2 DOSAGE AND ADMINISTRATION

Infusion given intravenously over no less than 15 minutes:

- Treatment of postmenopausal osteoporosis (2.2); treatment to increase bone mass in men with osteoporosis (2.4): treatment and prevention of glucocorticoid-induced osteoporosis (2.5): 5 mg once a year
- Prevention of postmenopausal osteoporosis: 5 mg once every 2 years (2.3)
- Treatment of Paget’s disease of bone: a single 5 mg infusion. Patients should receive 1500 mg elemental calcium and 800 international units vitamin D daily (2.6)

3 DOSAGE FORMS AND STRENGTHS

5 mg in a 100 mL ready-to-infuse solution (3)

4 CONTRAINDICATIONS

- Hypocalcemia (4)
- Patients with creatinine clearance less than 35 mL/min and in those with evidence of acute renal impairment (4, 5.3)
- Hypersensitivity to any component of Reclast (4, 6.2)

5 WARNINGS AND PRECAUTIONS

- Products Containing Same Active Ingredient: Patients receiving Zometa should not receive Reclast (5.1)
- Hypocalcemia may worsen during treatment. Patients must be adequately supplemented with calcium and vitamin D (5.2)
- Renal Impairment: A single dose should not exceed 5 mg and the duration of infusion should be no less than 15 minutes. Renal toxicity may be greater in patients with underlying renal impairment or with other risk factors, including advanced age or dehydration. Monitor creatinine clearance before each dose (2.7, 5.3)
- Osteonecrosis of the Jaw (ONJ) has been reported. All patients should have a routine oral exam by the prescriber prior to treatment (5.4)
- Atypical Fractures Including Femoral Fractures have been reported. Patients with thigh or groin pain should be evaluated to rule out a femoral fracture. Risk/benefit of continuing bisphosphonate therapy should be re-evaluated in these patients and interruption of bisphosphonate therapy should be considered (5.5)
- Severe Bone, Joint, and Muscle Pain may occur. Withhold future doses of Reclast if severe symptoms occur (5.6)

6 ADVERSE REACTIONS

The most common adverse reactions (greater than 10%) were pyrexia, myalgia, headache, arthralgia, pain in extremity (6.1). Other important adverse reactions were flu-like illness, nausea, vomiting, diarrhea (6.2), and eye inflammation (6.1).

To report SUSPECTED ADVERSE REACTIONS, contact Sandoz Inc. at 1-800-525-8747 or FDA at 1-800-FDA-1088 or www.fda.gov/medwatch.

7 DRUG INTERACTIONS

- Aminoglycosides: May lower serum calcium for prolonged periods (7.1)
- Loop Diuretics: May increase risk of hypocalcemia (7.2)
- Nephrotoxic Drugs: Use with caution (7.3)
- Drugs Primarily Excreted by the Kidney: Exposure may be increased with renal impairment. Monitor serum creatinine in patients at risk (7.4)

8 USE IN SPECIFIC POPULATIONS

- Pregnancy: Discontinue when pregnancy is recognized (8.1)
- Pediatric Use: Not indicated for use in pediatric patients (8.4)
- Geriatric Use: Special care to monitor renal function (8.5)

FULL PRESCRIBING INFORMATION

1 INDICATIONS AND USAGE

1.1 Treatment of Osteoporosis in Postmenopausal Women

Reclast is indicated for treatment of osteoporosis in postmenopausal women. In postmenopausal women with osteoporosis, diagnosed by bone mineral density (BMD) or prevalent vertebral fracture, Reclast reduces the incidence of fractures (hip, vertebral, and non-vertebral osteoporosis-related fractures). In patients at high risk of fracture, defined as a recent low-trauma hip fracture, Reclast reduces the incidence of new clinical fractures [see Clinical Studies (14.1)].

1.2 Prevention of Osteoporosis in Postmenopausal Women

Reclast is indicated for prevention of osteoporosis in postmenopausal women [see Clinical Studies (14.2)].

1.3 Osteoporosis in Men

Reclast is indicated for treatment to increase bone mass in men with osteoporosis [see Clinical Studies (14.3)].

1.4 Glucocorticoid-Induced Osteoporosis

Reclast is indicated for the treatment and prevention of glucocorticoid-induced osteoporosis in men and women who are either initiating or continuing systemic glucocorticoids in a daily dosage equivalent to 7.5 mg or greater of prednisone and who are expected to remain on glucocorticoids for at least 12 months [see Clinical Studies (14.4)].

1.5 Paget's Disease of Bone

Reclast is indicated for treatment of Paget's disease of bone in men and women. Treatment is indicated in patients with Paget’s disease of bone with elevations in serum alkaline phosphatase of two times or higher than the upper limit of the age-specific normal reference range, or those who are symptomatic, or those at risk for complications from their disease [see Clinical Studies (14.5)].

1.6 Important Limitations of Use

The safety and effectiveness of Reclast for the treatment of osteoporosis is based on clinical data of three years duration. The optimal duration of use has not been determined. All patients on bisphosphonate therapy should have the need for continued therapy reevaluated on a periodic basis. Patients at low-risk for fracture should be considered for drug discontinuation after 3 to 5 years of use. Patients who discontinue therapy should have their risk for fracture reevaluated periodically.

2 DOSAGE AND ADMINISTRATION

2.1 Important Administration Instructions

Reclast injection must be administered as an intravenous infusion over no less than 15 minutes.

- Patients must be appropriately hydrated prior to administration of Reclast [see Warnings and Precautions (5.3)].
- Parenteral drug products should be inspected visually for particulate matter and discoloration prior to administration, whenever solution and container permit.
- Intravenous infusion should be followed by a 10 mL normal saline flush of the intravenous line.
- Administration of acetaminophen following Reclast administration may reduce the incidence of acute-phase reaction symptoms.

2.2 Treatment of Osteoporosis in Postmenopausal Women

The recommended regimen is a 5 mg infusion once a year given intravenously over no less than 15 minutes.

2.3 Prevention of Osteoporosis in Postmenopausal Women

The recommended regimen is a 5 mg infusion given once every 2 years intravenously over no less than 15 minutes.

2.4 Osteoporosis in Men

The recommended regimen is a 5 mg infusion once a year given intravenously over no less than 15 minutes.

2.5 Treatment and Prevention of Glucocorticoid-Induced Osteoporosis

The recommended regimen is a 5 mg infusion once a year given intravenously over no less than 15 minutes.

2.6 Treatment of Paget’s Disease of Bone

The recommended dose is a 5 mg infusion. The infusion time must not be less than 15 minutes given over a constant infusion rate.

Re-treatment of Paget’s Disease

After a single treatment with Reclast in Paget’s disease an extended remission period is observed. Specific re-treatment data are not available. However, re-treatment with Reclast may be considered in patients who have relapsed, based on increases in serum alkaline phosphatase, or in those patients who failed to achieve normalization of their serum alkaline phosphatase, or in those patients with symptoms, as dictated by medical practice.

2.7 Laboratory Testing and Oral Examination Prior to Administration

- Prior to administration of each dose of Reclast, obtain a serum creatinine and creatinine clearance should be calculated based on actual body weight using Cockcroft-Gault formula before each Reclast dose. Reclast is contraindicated in patients with creatinine clearance less than 35 mL/min and in those with evidence of acute renal impairment. A 5 mg dose of Reclast administered intravenously is recommended for patients with creatinine clearance greater than or equal to 35 mL/min. There are no safety or efficacy data to support the adjustment of the Reclast dose based on baseline renal function. Therefore, no dose adjustment is required in patients with creatinine clearance greater than or equal to 35 mL/min [see Contraindications (4), Warnings and Precautions (5.3)].
- A routine oral examination should be performed by the prescriber prior to initiation of Reclast treatment [see Warnings and Precautions (5.4)].

2.8 Calcium and Vitamin D Supplementation

- Instruct patients being treated for Paget’s disease of bone on the importance of calcium and vitamin D supplementation in maintaining serum calcium levels, and on the symptoms of hypocalcemia. All patients should take 1500 mg elemental calcium daily in divided doses (750 mg two times a day, or 500 mg three times a day) and 800 international units vitamin D daily, particularly in the 2 weeks following Reclast administration [see Warnings and Precautions (5.2)].
- Instruct patients being treated for osteoporosis to take supplemental calcium and vitamin D if their dietary intake is inadequate. An average of at least 1200 mg calcium and 800-1000 international units vitamin D daily is recommended.

2.9 Method of Administration

The Reclast infusion time must not be less than 15 minutes given over a constant infusion rate.

The intravenous infusion should be followed by a 10 mL normal saline flush of the intravenous line.

Reclast solution for infusion must not be allowed to come in contact with any calcium or other divalent cation-containing solutions, and should be administered as a single intravenous solution through a separate vented infusion line.

If refrigerated, allow the refrigerated solution to reach room temperature before administration. After opening, the solution is stable for 24 hours at 2°C to 8°C (36°F to 46°F) [see How Supplied/Storage and Handling (16)].

3 DOSAGE FORMS AND STRENGTHS

5 mg in a 100 mL ready to infuse solution.

4 CONTRAINDICATIONS

Reclast is contraindicated in patients with the following conditions:

- Hypocalcemia [see Warnings and Precautions (5.2)]
- Creatinine clearance less than 35 mL/min and in those with evidence of acute renal impairment due to an increased risk of renal failure [see Warnings and Precautions (5.3)].
- Known hypersensitivity to zoledronic acid or any components of Reclast. Hypersensitivity reactions, including urticaria, angioedema, and anaphylactic reaction/shock have been reported [see Adverse Reactions (6.2)].

5 WARNINGS AND PRECAUTIONS

5.1 Drug Products With Same Active Ingredient

Reclast contains the same active ingredient found in Zometa, used for oncology indications, and a patient being treated with Zometa should not be treated with Reclast.

5.2 Hypocalcemia and Mineral Metabolism

Preexisting hypocalcemia and disturbances of mineral metabolism (e.g., hypoparathyroidism, thyroid surgery, parathyroid surgery; malabsorption syndromes, excision of small intestine) must be effectively treated before initiating therapy with Reclast. Clinical monitoring of calcium and mineral levels (phosphorus and magnesium) is highly recommended for these patients [see Contraindications (4)].

Hypocalcemia following Reclast administration is a significant risk in Paget’s disease. All patients should be instructed about the symptoms of hypocalcemia and the importance of calcium and vitamin D supplementation in maintaining serum calcium levels [see Dosage and Administration (2.8), Adverse Reactions (6.1), Patient Counseling Information (17)].

All osteoporosis patients should be instructed on the importance of calcium and vitamin D supplementation in maintaining serum calcium levels [see Dosage and Administration (2.8), Adverse Reactions (6.1), Patient Counseling Information (17)].

5.3 Renal Impairment

A single dose of Reclast should not exceed 5 mg and the duration of infusion should be no less than 15 minutes [see Dosage and Administration (2)].

Reclast is contraindicated in patients with creatinine clearance less than 35 mL/min and in those with evidence of acute renal impairment [see Contraindications (4)]. If history or physical signs suggest dehydration, Reclast therapy should be withheld until normovolemic status has been achieved [see Adverse Reactions (6.2)].

Reclast should be used with caution in patients with chronic renal impairment. Acute renal impairment, including renal failure, has been observed following the administration of zoledronic acid, especially in patients with preexisting renal compromise, advanced age, concomitant nephrotoxic medications, concomitant diuretic therapy, or severe dehydration occurring before or after Reclast administration. Acute renal failure (ARF) has been observed in patients after a single administration. Rare reports of hospitalization and/or dialysis or fatal outcome occurred in patients with underlying moderate to severe renal impairment or with any of the risk factors described in this section [see Adverse Reactions (6.2)]. Renal impairment may lead to increased exposure of concomitant medications and/or their metabolites that are primarily renally excreted [see Drug Interactions (7.4)].

Creatinine clearance should be calculated based on actual body weight using Cockcroft-Gault formula before each Reclast dose. Transient increase in serum creatinine may be greater in patients with impaired renal function; interim monitoring of creatinine clearance should be performed in at-risk patients. Elderly patients and those receiving diuretic therapy are at increased risk of acute renal failure. These patients should have their fluid status assessed and be appropriately hydrated prior to administration of Reclast. Reclast should be used with caution with other nephrotoxic drugs [see Drug Interactions (7.3)]. Consider monitoring creatinine clearance in patients at-risk for ARF who are taking concomitant medications that are primarily excreted by the kidney [see Drug Interactions (7.4)].

5.4 Osteonecrosis of the Jaw

Osteonecrosis of the jaw (ONJ) has been reported in patients treated with bisphosphonates, including zoledronic acid. Most cases have been in cancer patients treated with intravenous bisphosphonates undergoing dental procedures. Some cases have occurred in patients with postmenopausal osteoporosis treated with either oral or intravenous bisphosphonates. A routine oral examination should be performed by the prescriber prior to initiation of bisphosphonate treatment. A dental examination with appropriate preventive dentistry should be considered prior to treatment with bisphosphonates in patients with a history of concomitant risk factors (e.g., cancer, chemotherapy, angiogenesis inhibitors, radiotherapy, corticosteroids, poor oral hygiene, preexisting dental disease or infection, anemia, coagulopathy). The risk of ONJ may increase with duration of exposure to bisphosphonates. Concomitant administration of drugs associated with ONJ may increase the risk of developing ONJ.

While on treatment, patients with concomitant risk factors should avoid invasive dental procedures if possible. For patients who develop ONJ while on bisphosphonate therapy, dental surgery may exacerbate the condition. For patients requiring dental procedures, there are no data available to suggest whether discontinuation of bisphosphonate treatment reduces the risk of ONJ. The clinical judgment of the treating physician should guide the management plan of each patient based on individual benefit/risk assessment [see Adverse Reactions (6.1)].

5.5 Atypical Fractures Including Femoral Fractures

Atypical, low-energy, or low trauma fractures of the femoral shaft have been reported during treatment with bisphosphonates, including zolendronic acid, in patients with osteoporosis. Atypical femur and other fractures most commonly occur with minimal or no trauma to the affected area. These fractures occurred anywhere in the femoral shaft from just below the lesser trochanter to above the supracondylar flare and are transverse or short oblique in orientation without evidence of comminution. Atypical fractures of other bones have also been reported. They may be bilateral. These fractures can also occur in osteoporotic patients who have not been treated with bisphosphonates. Concomitant treatment with glucocorticoids may also induce these fractures.

Prodromal pain in the affected area, usually presenting as dull, aching thigh pain, weeks to months before a complete fracture occurs.

Any patient with a history of bisphosphonate exposure who presents with thigh or groin pain should be suspected of having an atypical fracture and should be evaluated to rule out an incomplete femur fracture. Bony pain in other locations should also be considered for evaluation of atypical fracture. Patients presenting with an atypical femur fracture should also be assessed for symptoms and signs of fracture in the contralateral limb. Risk/benefit of continuing bisphosphonate therapy should be re-evaluated in these patients and interruption of bisphosphonate therapy should be considered.

5.6 Musculoskeletal Pain

In post-marketing experience, severe and occasionally incapacitating bone, joint, and/or muscle pain have been infrequently reported in patients taking bisphosphonates, including Reclast. The time to onset of symptoms varied from one day to several months after starting the drug. Consider withholding future Reclast treatment if severe symptoms develop. Most patients had relief of symptoms after stopping. A subset had recurrence of symptoms when rechallenged with the same drug or another bisphosphonate [see Adverse Reactions (6.2)].

5.7 Patients With Asthma

While not observed in clinical trials with Reclast, there have been reports of bronchoconstriction in aspirin-sensitive patients receiving bisphosphonates. Use Reclast with caution in aspirin-sensitive patients.

6 ADVERSE REACTIONS

The following clinically significant adverse drug reactions are described elsewhere in the labeling:

- Drugs with Same Active Ingredient [see Warnings and Precautions (5.1)]
- Hypocalcemia and Mineral Metabolism [see Warnings and Precautions (5.2)]
- Renal Impairment [see Warnings and Precautions (5.3)]
- Osteonecrosis of the Jaw [see Warnings and Precautions (5.4)]
- Atypical Fractures Including Femoral Fractures [see Warnings and Precautions (5.5)]
- Musculoskeletal Pain [see Warnings and Precautions (5.6)]
- Patients with Asthma [see Warnings and Precautions (5.7)]

6.1 Clinical Trials Experience

Because clinical trials are conducted under widely varying conditions, adverse reaction rates observed in the clinical trials of a drug cannot be directly compared to rates in the clinical trials of another drug and may not reflect the rates observed in practice.

Treatment of Osteoporosis in Postmenopausal Women

The safety of Reclast in the treatment of postmenopausal osteoporosis was assessed in Study 1, a large, randomized, double-blind, placebo-controlled, multinational study of 7736 postmenopausal women aged 65 to 89 years with osteoporosis, diagnosed by BMD or the presence of a prevalent vertebral fracture. The duration of the trial was three years with 3862 patients exposed to Reclast and 3852 patients exposed to placebo administered once annually as a single 5 mg dose in 100 mL solution infused over at least 15 minutes, for a total of three doses. All women received 1000 to 1500 mg of elemental calcium plus 400 to 1200 international units of vitamin D supplementation per day.

The incidence of all-cause mortality was similar between groups: 3.4% in the Reclast group and 2.9% in the placebo group. The incidence of serious adverse events was 29.2% in the Reclast group and 30.1% in the placebo group. The percentage of patients who withdrew from the study due to adverse events was 5.4% and 4.8% for the Reclast and placebo groups, respectively.

The safety of Reclast in the treatment of osteoporosis patients with a recent (within 90 days) low-trauma hip fracture was assessed in Study 2, a randomized, double-blind, placebo-controlled, multinational endpoint-driven study of 2127 men and women aged 50 to 95 years; 1065 patients were randomized to Reclast and 1062 patients were randomized to placebo. Reclast was administered once annually as a single 5 mg dose in 100 mL solution infused over at least 15 minutes. The study continued until at least 211 patients had a confirmed clinical fracture in the study population who were followed for an average of approximately 2 years on study drug. Vitamin D levels were not routinely measured but a loading dose of vitamin D (50,000 to 125,000 international units orally or IM) was given to patients and they were started on 1000 to 1500 mg of elemental calcium plus 800 to 1200 international units of vitamin D supplementation per day for at least 14 days prior to the study drug infusions.

The incidence of all-cause mortality was 9.6% in the Reclast group and 13.3% in the placebo group. The incidence of serious adverse events was 38.3% in the Reclast group and 41.3% in the placebo group. The percentage of patients who withdrew from the study due to adverse events was 5.3% and 4.7% for the Reclast and placebo groups, respectively.

Adverse reactions reported in at least 2% of patients with osteoporosis and more frequently in the Reclast-treated patients than placebo-treated patients in either osteoporosis trial are shown below in Table 1.

Table 1. Adverse Reactions Occurring in Greater Than or Equal to 2.0% of Patients with Osteoporosis and More Frequently Than in Placebo-Treated Patients
 | Study 1 |  | Study 2
System Organ Class | 5 mg IV Reclast once per year % (N = 3862) | Placebo once per year % (N = 3852) | 5 mg IV Reclast once per year % (N = 1054) | Placebo once per year % (N = 1057)
Blood and the Lymphatic System Disorders
Anemia | 4.4 | 3.6 | 5.3 | 5.2
Metabolism and Nutrition Disorders
Dehydration | 0.6 | 0.6 | 2.5 | 2.3
Anorexia | 2.0 | 1.1 | 1.0 | 1.0
Nervous System Disorders
Headache | 12.4 | 8.1 | 3.9 | 2.5
Dizziness | 7.6 | 6.7 | 2.0 | 4.0
Ear and Labyrinth Disorders
Vertigo | 4.3 | 4.0 | 1.3 | 1.7
Cardiac Disorders
Atrial fibrillation | 2.4 | 1.9 | 2.8 | 2.6
Vascular Disorders
Hypertension | 12.7 | 12.4 | 6.8 | 5.4
Gastrointestinal Disorders
Nausea | 8.5 | 5.2 | 4.5 | 4.5
Diarrhea | 6.0 | 5.6 | 5.2 | 4.7
Vomiting | 4.6 | 3.2 | 3.4 | 3.4
Abdominal pain upper | 4.6 | 3.1 | 0.9 | 1.5
Dyspepsia | 4.3 | 4.0 | 1.7 | 1.6
Musculoskeletal, Connective Tissue and Bone Disorders
Arthralgia | 23.8 | 20.4 | 17.9 | 18.3
Myalgia | 11.7 | 3.7 | 4.9 | 2.7
Pain in extremity | 11.3 | 9.9 | 5.9 | 4.8
Shoulder pain | 6.9 | 5.6 | 0.0 | 0.0
Bone pain | 5.8 | 2.3 | 3.2 | 1.0
Neck pain | 4.4 | 3.8 | 1.4 | 1.1
Muscle spasms | 3.7 | 3.4 | 1.5 | 1.7
Osteoarthritis | 9.1 | 9.7 | 5.7 | 4.5
Musculoskeletal pain | 0.4 | 0.3 | 3.1 | 1.2
General Disorders and Administrative-Site Conditions
Pyrexia | 17.9 | 4.6 | 8.7 | 3.1
Influenza-like illness | 8.8 | 2.7 | 0.8 | 0.4
Fatigue | 5.4 | 3.5 | 2.1 | 1.2
Chills | 5.4 | 1.0 | 1.5 | 0.5
Asthenia | 5.3 | 2.9 | 3.2 | 3.0
Peripheral edema | 4.6 | 4.2 | 5.5 | 5.3
Pain | 3.3 | 1.3 | 1.5 | 0.5
Malaise | 2.0 | 1.0 | 1.1 | 0.5
Hyperthermia | 0.3 | < 0.1 | 2.3 | 0.3
Chest Pain | 1.3 | 1.1 | 2.4 | 1.8
Investigations
Creatinine renal clearance decreased | 2.0 | 2.4 | 2.1 | 1.7
Abbreviation: IV, intravenous or intravenously.

Renal Impairment

Treatment with intravenous bisphosphonates, including zoledronic acid, has been associated with renal impairment manifested as deterioration in renal function (i.e., increased serum creatinine) and in rare cases, acute renal failure. In the clinical trial for postmenopausal osteoporosis, patients with baseline creatinine clearance less than 30 mL/min (based on actual body weight), urine dipstick greater than or equal to 2+ protein or increase in serum creatinine of greater than 0.5 mg/dL during the screening visits were excluded. The change in creatinine clearance (measured annually prior to dosing) and the incidence of renal failure and impairment was comparable for both the Reclast and placebo treatment groups over 3 years, including patients with creatinine clearance between 30-60 mL/min at baseline. Overall, there was a transient increase in serum creatinine observed within 10 days of dosing in 1.8% of Reclast-treated patients versus 0.8% of placebo-treated patients which resolved without specific therapy [see Warnings and Precautions (5.3)].

Acute Phase Reaction

The signs and symptoms of acute phase reaction occurred in Study 1 following Reclast infusion, including fever (18%), myalgia (9%), flu-like symptoms (8%), headache (7%), and arthralgia (7%). The majority of these symptoms occurred within the first 3 days following the dose of Reclast and usually resolved within 3 days of onset but resolution could take up to 7-14 days. In Study 2, patients without a contraindication to acetaminophen were provided with a standard oral dose at the time of the IV infusion and instructed to use additional acetaminophen at home for the next 72 hours as needed. Reclast was associated with fewer signs and symptoms of a transient acute phase reaction in this trial: fever (7%) and arthralgia (3%). The incidence of these symptoms decreased with subsequent doses of Reclast.

Laboratory Findings

In Study 1, in women with postmenopausal osteoporosis, approximately 0.2% of patients had notable declines of serum calcium levels (less than 7.5 mg/dL) following Reclast administration. No symptomatic cases of hypocalcemia were observed. In Study 2, following pre-treatment with vitamin D, no patients had treatment emergent serum calcium levels below 7.5 mg/dL.

Injection-Site Reactions

In the osteoporosis trials, local reactions at the infusion site, such as itching, redness and/or pain have been reported in 0% to 0.7% of patients following the administration of Reclast and 0% to 0.5% of patients following administration of placebo.

Osteonecrosis of the Jaw

In the postmenopausal osteoporosis trial, Study 1, in 7736 patients, after initiation of therapy, symptoms consistent with ONJ occurred in one patient treated with placebo and one patient treated with Reclast. Both cases resolved after appropriate treatment [see Warnings and Precautions (5.4)]. No reports of ONJ were reported in either treatment group in Study 2.

Atrial Fibrillation

In the postmenopausal osteoporosis trial, Study 1, adjudicated serious adverse events of atrial fibrillation in the zoledronic acid treatment group occurred in 1.3% of patients (50 out of 3862) compared to 0.4% (17 out of 3852) in the placebo group. The overall incidence of all atrial fibrillation adverse events in the zoledronic acid treatment group was reported in 2.5% of patients (96 out of 3862) in the Reclast group vs. 1.9% of patients (75 out of 3852) in the placebo group. Over 90% of these events in both treatment groups occurred more than a month after the infusion. In an ECG sub-study, ECG measurements were performed on a subset of 559 patients before and 9 to 11 days after treatment. There was no difference in the incidence of atrial fibrillation between treatment groups suggesting these events were not related to the acute infusions. In Study 2, adjudicated serious adverse events of atrial fibrillation in the zoledronic acid treatment group occurred in 1.0% of patients (11 out of 1054) compared to 1.2% (13 out of 1057) in the placebo group demonstrating no difference between treatment groups.

Ocular Adverse Events

Cases of iritis/uveitis/episcleritis/conjunctivitis have been reported in patients treated with bisphosphonates, including zoledronic acid. In the osteoporosis trials, 1 (less than 0.1%) to 9 (0.2%) patients treated with Reclast and 0 (0%) to 1 (less than 0.1%) patient treated with placebo developed iritis/uveitis/episcleritis.

Prevention of Osteoporosis in Postmenopausal Women

The safety of Reclast in postmenopausal women with osteopenia (low bone mass) was assessed in a 2-year randomized, multi-center, double-blind, placebo-controlled study of 581 postmenopausal women aged greater than or equal to 45 years. Patients were randomized to one of three treatment groups: (1) Reclast given at randomization and Month 12 (n=198); (2) Reclast given at randomization and placebo at Month 12 (n=181); and (3) placebo given at randomization and Month 12 (n=202). Reclast was administered as a single 5 mg dose in 100 mL solution infused over at least 15 minutes. All women received 500 to 1200 mg elemental calcium plus 400 to 800 international units vitamin D supplementation per day.

The incidence of serious adverse events was similar for subjects given (1) Reclast at randomization and at Month 12 (10.6%), (2) Reclast at randomization and placebo given at Month 12 (9.4%), and (3) placebo at randomization and at Month 12 (11.4%). The percentages of patients who withdrew from the study due to adverse events were 7.1%, 7.2%, and 3.0% in the two Reclast groups and placebo group, respectively. Adverse reactions reported in at least 2% of patients with osteopenia and more frequently in the Reclast-treated patients than placebo-treated patients are shown in Table 2.

Table 2. Adverse Reactions Occurring in Greater Than or Equal to 2% of Patients with Osteopenia and More Frequently Than in Placebo-Treated Patients
System Organ Class | 5 mg IV Reclast once per year % (n = 198) | 5 mg IV Reclast once % (n = 181) | Placebo once per year % (n = 202)
Metabolism and nutrition Disorders
Anorexia | 2.0 | 0.6 | 0.0
Nervous system Disorders
Headache | 14.6 | 20.4 | 11.4
Dizziness | 7.6 | 6.1 | 3.5
Hypoesthesia | 5.6 | 2.2 | 2.0
Ear and Labyrinth Disorders
Vertigo | 2.0 | 1.7 | 1.0
Vascular Disorders
Hypertension | 5.1 | 8.3 | 6.9
Gastrointestinal Disorders
Nausea | 17.7 | 11.6 | 7.9
Diarrhea | 8.1 | 6.6 | 7.9
Vomiting | 7.6 | 5.0 | 4.5
Dyspepsia | 7.1 | 6.6 | 5.0
Abdominal pain [Combined abdominal pain, abdominal pain upper, and abdominal pain lower as one Adverse Drug Reaction (ADR).] | 8.6 | 6.6 | 7.9
Constipation | 6.6 | 7.2 | 6.9
Abdominal discomfort | 2.0 | 1.1 | 0.5
Abdominal distension | 2.0 | 0.6 | 0.0
Skin and Subcutaneous Tissue Disorders
Rash | 3.0 | 2.2 | 2.5
Musculoskeletal and Connective Tissue Disorders
Arthralgia | 27.3 | 18.8 | 19.3
Myalgia | 19.2 | 22.7 | 6.9
Back pain | 18.2 | 16.6 | 11.9
Pain in extremity | 11.1 | 16.0 | 9.9
Muscle spasms | 5.6 | 2.8 | 5.0
Musculoskeletal pain [Combined musculoskeletal pain and musculoskeletal chest pain as one ADR.] | 8.1 | 7.2 | 7.9
Bone pain | 5.1 | 3.3 | 1.0
Neck pain | 5.1 | 6.6 | 5.0
Arthritis | 4.0 | 2.2 | 1.5
Joint stiffness | 3.5 | 1.1 | 2.0
Joint swelling | 3.0 | 0.6 | 0.0
Flank pain | 2.0 | 0.6 | 0.0
Pain in jaw | 2.0 | 3.9 | 2.5
General Disorders and Administration-Site Conditions
Pain | 24.2 | 14.9 | 3.5
Pyrexia | 21.7 | 21.0 | 4.5
Chills | 18.2 | 18.2 | 3.0
Fatigue | 14.6 | 9.9 | 4.0
Asthenia | 6.1 | 2.8 | 1.0
Peripheral edema | 5.6 | 3.9 | 3.5
Non-cardiac chest pain | 3.5 | 7.7 | 3.0
Influenza-like illness | 1.5 | 3.3 | 2.0
Malaise | 1.0 | 2.2 | 0.5
Abbreviation: IV, intravenous or intravenously.

Ocular Adverse Events

Cases of iritis/uveitis/episcleritis/conjunctivitis have been reported in patients treated with bisphosphonates, including zoledronic acid. In the osteoporosis prevention trial, 4 (1.1%) patients treated with Reclast and 0 (0%) patients treated with placebo developed iritis/uveitis.

Acute Phase Reaction

In patients given Reclast at randomization and placebo at Month 12, Reclast was associated with signs and symptoms of an acute phase reaction: myalgia (20.4%), fever (19.3%), chills (18.2%), pain (13.8%), headache (13.3%), fatigue (8.3%), arthralgia (6.1%), pain in extremity (3.9%), influenza-like illness (3.3%), and back pain (1.7%), which occurred within the first 3 days following the dose of Reclast. The majority of these symptoms were mild to moderate and resolved within 3 days of the event onset but resolution could take up to 7-14 days.

Osteoporosis in Men

The safety of Reclast in men with osteoporosis or osteoporosis secondary to hypogonadism was assessed in a two year randomized, multicenter, double-blind, active controlled group study of 302 men aged 25 to 86 years. One hundred fifty three (153) patients were exposed to Reclast administered once annually with a 5 mg dose in 100 mL infused over 15 minutes for up to a total of two doses, and 148 patients were exposed to a commercially-available oral weekly bisphosphonate (active control) for up to two years. All participants received 1000 mg of elemental calcium plus 800 to 1000 international units of vitamin D supplementation per day.

The incidence of all-cause mortality (one in each group) and serious adverse events were similar between the Reclast and active control treatment groups. The percentage of patients experiencing at least one adverse event was comparable between the Reclast and active control groups, with the exception of a higher incidence of post-dose symptoms in the Reclast group that occurred within 3 days after infusion. The overall safety and tolerability of Reclast was similar to the active control.

Adverse reactions reported in at least 2% of men with osteoporosis and more frequently in the Reclast-treated patients than the active control-treated patients and either (1) not reported in the postmenopausal osteoporosis treatment trial or (2) reported more frequently in the trial of osteoporosis in men are presented in Table 3. Therefore, Table 3 should be viewed in conjunction with Table 1.

Table 3: Adverse Reactions Occurring in Greater Than or Equal to 2% of Men with Osteoporosis and More Frequently in the Reclast-Treated Patients Than the Active Control-Treated Patients and Either (1) Not Reported in the Postmenopausal Osteoporosis Treatment Trial or (2) Reported More Frequently in This Trial
System Organ Class | 5 mg IV Reclast once per year % (N = 153) | Active Control once weekly % (N = 148)
Nervous System Disorders
Headache | 15.0 | 6.1
Lethargy | 3.3 | 1.4
Eye Disorders
Eye pain | 2.0 | 0.0
Cardiac Disorders
Atrial fibrillation | 3.3 | 2.0
Palpitations | 2.6 | 0.0
Respiratory, Thoracic and Mediastinal Disorders
Dyspnea | 6.5 | 4.7
Abdominal pain [Combined abdominal pain, abdominal pain upper, and abdominal pain lower as one Adverse Drug Reaction (ADR).] | 7.9 | 4.1
Skin and Subcutaneous Tissue Disorders
Hyperhidrosis | 2.6 | 2.0
Musculoskeletal, Connective Tissue and Bone Disorders
Myalgia | 19.6 | 6.8
Musculoskeletal pain [Combined musculoskeletal pain and musculoskeletal chest pain as one ADR.] | 12.4 | 10.8
Musculoskeletal stiffness | 4.6 | 0.0
Renal and Urinary Disorders
Blood creatinine increased | 2.0 | 0.7
General Disorders and Administrative-Site Conditions
Fatigue | 17.6 | 6.1
Pain | 11.8 | 4.1
Chills | 9.8 | 2.7
Influenza-like illness | 9.2 | 2.0
Malaise | 7.2 | 0.7
Acute phase reaction | 3.9 | 0.0
Investigations
C-reactive protein increased | 4.6 | 1.4
Abbreviation: IV, intravenous or intravenously.

Renal Impairment

Creatinine clearance was measured annually prior to dosing and changes in long-term renal function over 24 months were comparable in the Reclast and active control groups [see Warnings and Precautions (5.3)].

Acute Phase Reaction

Reclast was associated with signs and symptoms of an acute phase reaction: myalgia (17.1%), fever (15.7%), fatigue (12.4%), arthralgia (11.1%), pain (10.5%), chills (9.8%), headache (9.8%), influenza-like illness (8.5%), malaise (5.2%), and back pain (3.3%), which occurred within the first 3 days following the dose of Reclast. The majority of these symptoms were mild to moderate and resolved within 3 days of the event onset but resolution could take up to 7-14 days. The incidence of these symptoms decreased with subsequent doses of Reclast.

Atrial Fibrillation

The incidence of all atrial fibrillation adverse events in the Reclast treatment group was 3.3% (5 out of 153) compared to 2.0% (3 out of 148) in the active control group. However, there were no patients with adjudicated serious adverse events of atrial fibrillation in the Reclast treatment group.

Laboratory Findings

There were no patients who had treatment emergent serum calcium levels below 7.5 mg/dL.

Injection-Site Reactions

There were 4 patients (2.6%) on Reclast vs. 2 patients (1.4%) on active control with local-site reactions.

Osteonecrosis of the Jaw

In this trial, there were no cases of ONJ [see Warnings and Precautions (5.4)].

Glucocorticoid-Induced Osteoporosis

The safety of Reclast in men and women in the treatment and prevention of glucocorticoid-induced osteoporosis was assessed in a randomized, multicenter, double-blind, active controlled, stratified study of 833 men, and women aged 18 to 85 years treated with greater than or equal to 7.5 mg/day oral prednisone (or equivalent). Patients were stratified according to the duration of their pre-study corticosteroid therapy: less than or equal to 3 months prior to randomization (prevention subpopulation), and greater than 3 months prior to randomization (treatment subpopulation).

The duration of the trial was one year with 416 patients exposed to Reclast administered once as a single 5 mg dose in 100 mL infused over 15 minutes, and 417 patients exposed to a commercially-available oral daily bisphosphonate (active control) for one year. All participants received 1000 mg of elemental calcium plus 400 to 1000 international units of vitamin D supplementation per day.

The incidence of all-cause mortality was similar between treatment groups: 0.9% in the Reclast group and 0.7% in the active control group. The incidence of serious adverse events was similar between the Reclast treatment and prevention groups, 18.4% and 18.1%, respectively, and the active control treatment and prevention groups, 19.8% and 16.0%, respectively. The percentage of subjects who withdrew from the study due to adverse events was 2.2% in the Reclast group vs. 1.4% in the active control group. The overall safety and tolerability were similar between Reclast and active control groups with the exception of a higher incidence of post-dose symptoms in the Reclast group that occurred within 3 days after infusion. The overall safety and tolerability profile of Reclast in glucocorticoid-induced osteoporosis was similar to the adverse events reported in the Reclast postmenopausal osteoporosis clinical trial.

Adverse reactions reported in at least 2% of patients that were either not reported in the postmenopausal osteoporosis treatment trial or reported more frequently in the treatment and prevention of glucocorticoid-induced osteoporosis trial included the following: abdominal pain (Reclast 7.5%; active control 5.0%), and musculoskeletal pain (Reclast 3.1%; active control 1.7%). Other musculoskeletal events included back pain (Reclast 4.3%, active control 6.2%), bone pain (Reclast 3.1%, active control 2.2%), and pain in the extremity (Reclast 3.1%, active control 1.2%). In addition, the following adverse events occurred more frequently than in the postmenopausal osteoporosis trial: nausea (Reclast 9.6%; active control 8.4%), and dyspepsia (Reclast 5.5%; active control 4.3%).

Renal Impairment

Renal function measured prior to dosing and at the end of the 12-month study was comparable in the Reclast and active control groups [see Warnings and Precautions (5.3)].

Acute Phase Reaction

Reclast was associated with signs and symptoms of a transient acute phase reaction that was similar to that seen in the Reclast postmenopausal osteoporosis clinical trial.

Atrial Fibrillation

The incidence of atrial fibrillation adverse events was 0.7% (3 of 416) in the Reclast group compared to no adverse events in the active control group. All subjects had a prior history of atrial fibrillation and no cases were adjudicated as serious adverse events. One patient had atrial flutter in the active control group.

Laboratory Findings

There were no patients who had treatment emergent serum calcium levels below 7.5 mg/dL.

Injection-Site Reactions

There were no local reactions at the infusion site.

Osteonecrosis of the Jaw

In this trial there were no cases of ONJ [see Warnings and Precautions (5.4)].

Paget’s Disease of Bone

In the Paget’s disease trials, two 6-month, double-blind, comparative, multinational studies of 349 men, and women aged greater than 30 years with moderate to severe disease and with confirmed Paget’s disease of bone, 177 patients were exposed to Reclast and 172 patients exposed to risedronate. Reclast was administered once as a single 5 mg dose in 100 mL solution infused over at least 15 minutes. Risedronate was given as an oral daily dose of 30 mg for 2 months.

The incidence of serious adverse events was 5.1% in the Reclast group and 6.4% in the risedronate group. The percentage of patients who withdrew from the study due to adverse events was 1.7% and 1.2% for the Reclast and risedronate groups, respectively.

Adverse reactions occurring in at least 2% of the Paget’s patients receiving Reclast (single 5 mg intravenous infusion) or risedronate (30 mg oral daily dose for 2 months) over a 6-month study period are listed by system organ class in Table 4.

Table 4. Adverse Reactions Reported in at Least 2% of Paget’s Patients Receiving Reclast (Single 5 mg Intravenous Infusion) or Risedronate (Oral 30 mg Daily for 2 Months) Over a 6-Month Follow-up Period
System Organ Class | 5 mg IV Reclast % (N = 177) | 30 mg/day x 2 Months risedronate % (N = 172)
Infections and Infestations
Influenza | 7 | 5
Metabolism and Nutrition Disorders
Hypocalcemia | 3 | 1
Anorexia | 2 | 2
Nervous System Disorders
Headache | 11 | 10
Dizziness | 9 | 4
Lethargy | 5 | 1
Paresthesia | 2 | 0
Respiratory, Thoracic and Mediastinal Disorders
Dyspnea | 5 | 1
Gastrointestinal Disorders
Nausea | 9 | 6
Diarrhea | 6 | 6
Constipation | 6 | 5
Dyspepsia | 5 | 4
Abdominal distension | 2 | 1
Abdominal pain | 2 | 2
Vomiting | 2 | 2
Abdominal pain upper | 1 | 2
Skin and Subcutaneous Tissue Disorders
Rash | 3 | 2
Musculoskeletal, Connective Tissue and Bone Disorders
Arthralgia | 9 | 11
Bone pain | 9 | 5
Myalgia | 7 | 4
Back pain | 4 | 7
Musculoskeletal stiffness | 2 | 1
General Disorders and Administrative-Site Conditions
Influenza-like illness | 11 | 6
Pyrexia | 9 | 2
Fatigue | 8 | 4
Rigors | 8 | 1
Pain | 5 | 4
Peripheral edema | 3 | 1
Asthenia | 2 | 1
Abbreviation: IV, intravenous or intravenously.

Laboratory Findings

In the Paget’s disease trials, early, transient decreases in serum calcium and phosphate levels were observed. Approximately 21% of patients had serum calcium levels less than 8.4 mg/dL 9-11 days following Reclast administration.

Renal Impairment

In clinical trials in Paget’s disease, there were no cases of renal deterioration following a single 5 mg 15-minute infusion [see Warnings and Precautions (5.3)].

Acute Phase Reaction

The signs and symptoms of acute phase reaction (influenza-like illness, pyrexia, myalgia, arthralgia, and bone pain) were reported in 25% of patients in the Reclast-treated group compared to 8% in the risedronate-treated group. Symptoms usually occur within the first 3 days following Reclast administration. The majority of these symptoms resolved within 4 days of onset.

Osteonecrosis of the Jaw

Osteonecrosis of the jaw has been reported with zoledronic acid [see Warnings and Precautions (5.4)].

6.2 Post-Marketing Experience

Because these reactions are reported voluntarily from a population of uncertain size, it is not always possible to reliably estimate their frequency or establish a causal relationship to drug exposure.

The following adverse reactions have been identified during post approval use of Reclast or bisphosphonate products:

Acute Phase Reactions

Fever, headache, flu-like symptoms, nausea, vomiting, diarrhea, arthralgia, and myalgia. Symptoms may be significant and lead to dehydration.

Acute Renal Failure

Acute renal failure requiring hospitalization and/or dialysis or with a fatal outcome have been rarely reported. Increased serum creatinine was reported in patients with 1) underlying renal disease, 2) dehydration secondary to fever, sepsis, gastrointestinal losses, or diuretic therapy, or 3) other risk factors, such as advanced age, or concomitant nephrotoxic drugs in the post-infusion period. Transient rise in serum creatinine can be correctable with intravenous fluids.

Allergic Reactions

Allergic reactions with intravenous zoledronic acid, including anaphylactic reaction/shock, urticaria, angioedema, Stevens-Johnson syndrome, toxic epidermal necrolysis, and bronchoconstriction have been reported.

Asthma Exacerbations

Asthma exacerbations have been reported.

Hypocalcemia

Hypocalcemia has been reported.

Hypophosphatemia

Hypophosphatemia has been reported.

Osteonecrosis of the Jaw

Osteonecrosis of the jaw has been reported.

Osteonecrosis of Other Bones

Cases of osteonecrosis of other bones (including femur, hip, knee, ankle, wrist and humerus) have been reported; causality has not been determined in the population treated with Reclast.

Musculoskeletal

Low-energy femoral shaft and subtrochanteric fractures, and atypical fractures of other bones [see Warnings and

Precautions (5.5)]

Ocular Adverse Events

Cases of the following events have been reported: conjunctivitis, iritis, iridocyclitis, uveitis, episcleritis, scleritis, and orbital inflammation/edema.

Other

Hypotension in patients with underlying risk factors has been reported.

7 DRUG INTERACTIONS

No in vivo drug interaction studies have been performed for Reclast. In vitro and ex vivo studies showed low affinity of zoledronic acid for the cellular components of human blood. In vitro mean zoledronic acid protein binding in human plasma ranged from 28% at 200 ng/mL to 53% at 50 ng/mL. In vivo studies showed that zoledronic acid is not metabolized, and is excreted into the urine as the intact drug.

7.1 Aminoglycosides

Caution is advised when bisphosphonates, including zoledronic acid, are administered with aminoglycosides, since these agents may have an additive effect to lower serum calcium level for prolonged periods. This effect has not been reported in zoledronic acid clinical trials.

7.2 Loop Diuretics

Caution should also be exercised when Reclast is used in combination with loop diuretics due to an increased risk of hypocalcemia.

7.3 Nephrotoxic Drugs

Caution is indicated when Reclast is used with other potentially nephrotoxic drugs, such as nonsteroidal anti-inflammatory drugs (NSAIDs).

7.4 Drugs Primarily Excreted by the Kidney

Renal impairment has been observed following the administration of zoledronic acid in patients with preexisting renal compromise or other risk factors [see Warnings and Precautions (5.3)]. In patients with renal impairment, the exposure to concomitant medications that are primarily renally excreted (e.g., digoxin) may increase. Consider monitoring serum creatinine in patients at risk for renal impairment who are taking concomitant medications that are primarily excreted by the kidney.

8 USE IN SPECIFIC POPULATIONS

8.1 Pregnancy

Risk Summary

Available data on the use of Reclast in pregnant women are insufficient to inform a drug-associated risk of adverse maternal or fetal outcomes. Discontinue Reclast when pregnancy is recognized.

In animal reproduction studies, daily subcutaneous administration of zoledronic acid to pregnant rats during organogenesis resulted in increases in fetal skeletal, visceral, and external malformations, decreases in postimplantation survival, and decreases in viable fetuses and fetal weight starting at doses equivalent to 2 times the recommended human 5 mg intravenous dose (based on AUC). Subcutaneous administration of zoledronic acid to rabbits during organogenesis did not cause adverse fetal effects at up to 0.4 times the human 5 mg intravenous dose (based on body surface area, mg/m^2), but resulted in maternal mortality and abortion associated with hypocalcemia starting at doses equivalent to 0.04 times the human 5 mg intravenous dose. Subcutaneous dosing of female rats from before mating through gestation and lactation and allowed to deliver caused maternal dystocia and periparturient mortality, increases in stillbirths and neonatal deaths, and reduced pup body weight starting at doses equivalent to 0.1 times the human 5 mg intravenous dose (based on AUC) (see Data).

Bisphosphonates are incorporated into the bone matrix, from which they are gradually released over a period of years. The amount of bisphosphonate incorporated into adult bone, and available for release into the systemic circulation is directly related to the dose and duration of bisphosphonate use. Consequently, based on the mechanism of action of bisphosphonates, there is a potential risk of fetal harm, predominantly skeletal, if a woman becomes pregnant after completing a course of bisphosphonate therapy. The impact of variables, such as time between cessation of bisphosphonate therapy to conception, the particular bisphosphonate used, and the route of administration (intravenous versus oral) on the risk has not been studied.

The estimated background risk of major birth defects and miscarriage for the indicated populations is unknown. All pregnancies have a background risk of birth defects, loss, or other adverse outcomes. In the U.S. general population, the estimated background risks of major birth defects and miscarriage in clinically recognized pregnancies is 2%-4% and 15%-20%, respectively.

Data

Animal Data

In pregnant rats given daily subcutaneous doses of zoledronic acid of 0.1, 0.2, or 0.4 mg/kg during organogenesis, fetal skeletal, visceral, and external malformations, increases in pre-and post-implantation loss, and decreases in viable fetuses and fetal weight were observed at 0.2 and 0.4 mg/kg/day (equivalent to 2 and 4 times the human 5 mg intravenous dose, based on AUC). Adverse fetal skeletal effects at 0.4 mg/kg/day (4 times the human 5 mg dose) included unossified or incompletely ossified bones, thickened, curved or shortened bones, wavy ribs, and shortened jaw. Other adverse fetal effects at this dose included reduced lens, rudimentary cerebellum, reduction or absence of liver lobes, reduction of lung lobes, vessel dilation, cleft palate, and edema. Skeletal variations were observed in all groups starting at 0.1 mg/kg/day (1.2 times the human 5 mg dose). Signs of maternal toxicity, including reduced body weight and food consumption were observed at 0.4 mg/kg/day (4 times the human 5 mg dose).

In pregnant rabbits given daily subcutaneous doses of zoledronic acid of 0.01, 0.03, or 0.1 mg/kg during gestation, no adverse fetal effects were observed up to 0.1 mg/kg/day (0.4 times the human 5 mg intravenous dose, based on body surface area, mg/m^2). Maternal mortality and abortion were observed in all dose groups (starting at 0.04 times the human 5 mg dose). Adverse maternal effects were associated with drug-induced hypocalcemia.

In female rats given daily subcutaneous doses of 0.01, 0.03, or 0.1 mg/kg, beginning 15 days before mating and continuing through gestation, parturition and lactation, dystocia and periparturient mortality were observed in pregnant rats allowed to deliver starting at 0.01 mg/kg/day (0.1 times the human 5 mg intravenous dose, based on AUC). Also, there was an increase in stillbirths and a decrease in neonate survival starting at 0.03 mg/kg/day (0.3 times the human 5 mg dose), while the number of viable newborns and pup body weight on postnatal Day 7 were decreased at 0.1 mg/kg/day (equivalent to the human 5 mg dose). Maternal and neonatal deaths were considered related to drug-induced periparturient hypocalcemia.

8.2 Lactation

Risk Summary

There are no data on the presence of zoledronic acid in human milk, the effects on the breast-fed infant, or the effects on milk production. The developmental and health benefits of breastfeeding should be considered along with the mother’s clinical need for Reclast and any potential adverse effects on the breast-fed child from Reclast, or from the underlying maternal condition.

8.3 Females and Males of Reproductive Potential

Infertility

There are no data available in humans. Female fertility may be impaired based on animal studies demonstrating adverse effects of Reclast on fertility parameters [see Nonclinical Toxicology (13.1)].

8.4 Pediatric Use

Reclast is not indicated for use in children.

The safety and effectiveness of zoledronic acid was studied in a one-year active controlled trial of 152 pediatric subjects (74 receiving zoledronic acid). The enrolled population was subjects with severe osteogenesis imperfecta, aged 1 to 17 years, 55% male, 84% Caucasian, with a mean lumbar spine BMD of 0.431 gm/cm^2, which is 2.7 standard deviations below the mean for age-matched controls (BMD Z-score of -2.7). At one year, increases in BMD were observed in the zoledronic acid treatment group. However, changes in BMD in individual patients with severe osteogenesis imperfecta did not necessarily correlate with the risk for fracture or the incidence or severity of chronic bone pain. The adverse events observed with zoledronic acid use in children did not raise any new safety findings beyond those previously seen in adults treated for Paget’s disease of bone and treatment of osteoporosis, including ONJ and renal impairment. However, adverse reactions seen more commonly in pediatric patients included pyrexia (61%), arthralgia (26%), hypocalcemia (22%), and headache (22%). These reactions, excluding arthralgia, occurred most frequently within three days after the first infusion and became less common with repeat dosing. No cases of ONJ or renal impairment were observed in this study. Because of long-term retention in bone, Reclast should only be used in children if the potential benefit outweighs the potential risk.

Plasma zoledronic acid concentration data was obtained from 10 patients with severe osteogenesis imperfecta (4 in the age group of 3 to 8 years and 6 in the age group of 9 to 17 years) infused with 0.05 mg/kg dose over 30 minutes. Mean Cmax and AUC(0-last) was 167 ng/mL and 220 ng.h/mL, respectively. The plasma concentration time profile of zoledronic acid in pediatric patients represent a multi-exponential decline, as observed in adult cancer patients at an approximately equivalent mg/kg dose.

8.5 Geriatric Use

The combined osteoporosis trials included 4863 Reclast-treated patients who were at least 65 years of age, while 2101 patients were at least 75 years old. No overall differences in efficacy or safety were observed between patients under 75 years of age with those at least 75 years of age, except that the acute phase reactions occurred less frequently in the older patients.

Of the patients receiving Reclast in the osteoporosis study in men, glucocorticoid-induced osteoporosis, and Paget’s disease studies, 83, 116, and 132 patients, respectively were 65 years of age or over, while 24, 29, and 68 patients, respectively were at least 75 years of age.

However, because decreased renal function occurs more commonly in the elderly, special care should be taken to monitor renal function.

8.6 Renal Impairment

Reclast is contraindicated in patients with creatinine clearance less than 35 mL/min and in those with evidence of acute renal impairment. There are no safety or efficacy data to support the adjustment of the Reclast dose based on baseline renal function. Therefore, no dosage adjustment is required in patients with a creatinine clearance of greater than or equal to 35 mL/min [see Warnings and Precautions (5.3), Clinical Pharmacology (12.3)]. Risk of acute renal failure may increase with underlying renal disease and dehydration secondary to fever, sepsis, gastrointestinal losses, diuretic therapy, advanced age, etc. [see Adverse Reactions (6.2)].

8.7 Hepatic Impairment

Reclast is not metabolized in the liver. No clinical data are available for use of Reclast in patients with hepatic impairment.

10 OVERDOSAGE

Clinical experience with acute overdosage of zoledronic acid (Reclast) solution for intravenous infusion is limited. Patients who have received doses higher than those recommended should be carefully monitored. Overdosage may cause clinically significant renal impairment, hypocalcemia, hypophosphatemia, and hypomagnesemia. Clinically relevant reductions in serum levels of calcium, phosphorus, and magnesium should be corrected by intravenous administration of calcium gluconate, potassium or sodium phosphate, and magnesium sulfate, respectively.

Single doses of Reclast should not exceed 5 mg and the duration of the intravenous infusion should be no less than 15 minutes [see Dosage and Administration (2)].

11 DESCRIPTION

Reclast contains zoledronic acid, a bisphosphonic acid which is an inhibitor of osteoclastic bone resorption. Zoledronic acid is designated chemically as (1-Hydroxy-2-imidazol-1-yl-phosphonoethyl) phosphonic acid monohydrate and its structural formula is:

Zoledronic acid monohydrate is a white crystalline powder. Its molecular formula is C5H10N2O7P2 • H2O and a molar mass of 290.1 g/mol. Zoledronic acid monohydrate is highly soluble in 0.1N sodium hydroxide solution, sparingly soluble in water and 0.1N hydrochloric acid, and practically insoluble in organic solvents. The pH of the Reclast solution for infusion is approximately 6.0–7.0.

Reclast Injection is available as a sterile solution in bottles for intravenous infusion. One bottle with 100 mL solution contains 5.330 mg of zoledronic acid monohydrate, equivalent to 5 mg zoledronic acid on an anhydrous basis.

Inactive Ingredients: 4950 mg of mannitol, USP; and 30 mg of sodium citrate, USP.

12 CLINICAL PHARMACOLOGY

12.1 Mechanism of Action

Reclast is a bisphosphonate and acts primarily on bone. It is an inhibitor of osteoclast-mediated bone resorption.

The selective action of bisphosphonates on bone is based on their high affinity for mineralized bone. Intravenously administered zoledronic acid rapidly partitions to bone and localizes preferentially at sites of high bone turnover. The main molecular target of zoledronic acid in the osteoclast is the enzyme farnesyl pyrophosphate synthase. The relatively long duration of action of zoledronic acid is attributable to its high binding affinity to bone mineral.

12.2 Pharmacodynamics

In the osteoporosis treatment trial, the effect of Reclast treatment on markers of bone resorption (serum beta-C-telopeptides [b-CTx]) and bone formation (bone specific alkaline phosphatase [BSAP], serum N-terminal propeptide of type I collagen [P1NP]) was evaluated in patients (subsets ranging from 517 to 1246 patients) at periodic intervals. Treatment with a 5 mg annual dose of Reclast reduces bone turnover markers to the pre-menopausal range with an approximate 55% reduction in b-CTx, a 29% reduction in BSAP and a 52% reduction in P1NP over 36 months. There was no progressive reduction of bone turnover markers with repeated annual dosing.

12.3 Pharmacokinetics

Pharmacokinetic data in patients with osteoporosis and Paget's disease of bone are not available.

Distribution: Single or multiple (every 28 days) 5-minute or 15-minute infusions of 2, 4, 8, or 16 mg zoledronic acid were given to 64 patients with cancer and bone metastases. The post-infusion decline of zoledronic acid concentrations in plasma was consistent with a triphasic process showing a rapid decrease from peak concentrations at end-of-infusion to less than 1% of Cmax 24 hours post infusion with population half-lives of t1/2α 0.24 hour and t1/2β 1.87 hours for the early disposition phases of the drug. The terminal elimination phase of zoledronic acid was prolonged, with very low concentrations in plasma between Days 2 and 28 post infusion, and a terminal elimination half-life t1/2γ of 146 hours. The area under the plasma concentration versus time curve (AUC0-24h) of zoledronic acid was dose proportional from 2 to 16 mg. The accumulation of zoledronic acid measured over three cycles was low, with mean AUC0-24h ratios for cycles 2 and 3 versus 1 of 1.13 ± 0.30 and 1.16 ± 0.36, respectively.

In vitro and ex vivo studies showed low affinity of zoledronic acid for the cellular components of human blood. In vitro mean zoledronic acid protein binding in human plasma ranged from 28% at 200 ng/mL to 53% at 50 ng/mL.

Metabolism: Zoledronic acid does not inhibit human P450 enzymes in vitro. Zoledronic acid does not undergo biotransformation in vivo. In animal studies, less than 3% of the administered intravenous dose was found in the feces, with the balance either recovered in the urine or taken up by bone, indicating that the drug is eliminated intact via the kidney. Following an intravenous dose of 20 nCi ^14C-zoledronic acid in a patient with cancer and bone metastases, only a single radioactive species with chromatographic properties identical to those of parent drug was recovered in urine, which suggests that zoledronic acid is not metabolized.

Excretion: In 64 patients with cancer and bone metastases on average (± SD) 39 ± 16% of the administered zoledronic acid dose was recovered in the urine within 24 hours, with only trace amounts of drug found in urine post Day 2. The cumulative percent of drug excreted in the urine over 0-24 hours was independent of dose. The balance of drug not recovered in urine over 0-24 hours, representing drug presumably bound to bone, is slowly released back into the systemic circulation, giving rise to the observed prolonged low plasma concentrations. The 0-24 hour renal clearance of zoledronic acid was 3.7 ± 2.0 L/h.

Zoledronic acid clearance was independent of dose but dependent upon the patient’s creatinine clearance. In a study in patients with cancer and bone metastases, increasing the infusion time of a 4 mg dose of zoledronic acid from 5 minutes (n=5) to 15 minutes (n=7) resulted in a 34% decrease in the zoledronic acid concentration at the end of the infusion ([mean ± SD] 403 ± 118 ng/mL vs. 264 ± 86 ng/mL) and a 10% increase in the total AUC (378 ± 116 ng x h/mL vs. 420 ± 218 ng x h/mL). The difference between the AUC means was not statistically significant.

Specific Populations

Pediatrics: Reclast is not indicated for use in children [see Pediatric Use (8.4)].

Geriatrics: The pharmacokinetics of zoledronic acid was not affected by age in patients with cancer and bone metastases whose age ranged from 38 years to 84 years.

Race: The pharmacokinetics of zoledronic acid was not affected by race in patients with cancer and bone metastases.

Hepatic Impairment: No clinical studies were conducted to evaluate the effect of hepatic impairment on the pharmacokinetics of zoledronic acid.

Renal Impairment: The pharmacokinetic studies conducted in 64 cancer patients represented typical clinical populations with normal to moderately-impaired renal function. Compared to patients with creatinine clearance greater than 80 mL/min (N = 37), patients with creatinine clearance = 50-80 mL/min (N = 15) showed an average increase in plasma AUC of 15%, whereas patients with creatinine clearance = 30-50 mL/min (N = 11) showed an average increase in plasma AUC of 43%. No dosage adjustment is required in patients with a creatinine clearance of greater than or equal to 35 mL/min. Reclast is contraindicated in patients with creatinine clearance less than 35 mL/min and in those with evidence of acute renal impairment due to an increased risk of renal failure [see Contraindications (4), Warnings and Precautions (5.3), Use in Specific Populations (8.6)].

13 NONCLINICAL TOXICOLOGY

13.1 Carcinogenesis, Mutagenesis, Impairment of Fertility

Carcinogenesis: Lifetime carcinogenicity bioassays were conducted in mice and rats. Mice were given daily oral doses of zoledronic acid of 0.1, 0.5, or 2.0 mg/kg/day for 2 years. There was an increased incidence of Harderian gland adenomas in males and females in all treatment groups (starting at doses equivalent to 0.002 times the human 5 mg intravenous dose, based on body surface area, mg/m^2). Rats were given daily oral doses of zoledronic acid of 0.1, 0.5, or 2.0 mg/kg/day for 2 years. No increased incidence of tumors was observed at any dose (up to 0.1 times the human intravenous dose of 5 mg, based on body surface area, mg/m^2).

Mutagenesis: Zoledronic acid was not genotoxic in the Ames bacterial mutagenicity assay, in the Chinese hamster ovary cell assay, or in the Chinese hamster gene mutation assay, with or without metabolic activation. Zoledronic acid was not genotoxic in the in vivo rat micronucleus assay.

Impairment of Fertility: Female rats were given daily subcutaneous doses of zoledronic acid of 0.01, 0.03, or 0.1 mg/kg beginning 15 days before mating and continuing through gestation. Inhibition of ovulation and a decrease in the number of pregnant rats were observed at 0.1 mg/kg/day (equivalent to the human 5 mg intravenous dose, based on AUC). An increase in preimplantation loss and a decrease in the number of implantations and live fetuses were observed at 0.03 and 1 mg/kg/day (0.3 to 1 times the human 5 mg human intravenous dose).

13.2 Animal Pharmacology

Bone Safety Studies: Zoledronic acid is a potent inhibitor of osteoclastic bone resorption. In the ovariectomized rat, single IV doses of zoledronic acid of 4-500 mcg/kg (0.1 to 3.5 times the human 5 mg intravenous dose, based on body surface area, mg/m^2) suppressed bone turnover and protected against trabecular bone loss, cortical thinning and the reduction in vertebral and femoral bone strength in a dose-dependent manner. At a dose equivalent to human exposure at the 5 mg intravenous dose, the effect persisted for 8 months, which corresponds to approximately 8 remodeling cycles or 3 years in humans.

In ovariectomized rats and monkeys, weekly treatment with zoledronic acid dose-dependently suppressed bone turnover and prevented the decrease in cancellous and cortical BMD and bone strength, at yearly cumulative doses up to 3.5 times the human 5 mg intravenous dose, based on body surface area, mg/m^2. Bone tissue was normal and there was no evidence of a mineralization defect, no accumulation of osteoid, and no woven bone.

14 CLINICAL STUDIES

14.1 Treatment of Postmenopausal Osteoporosis

Study 1: The efficacy and safety of Reclast in the treatment of postmenopausal osteoporosis was demonstrated in Study 1, a randomized, double-blind, placebo-controlled, multinational study of 7736 women aged 65 to 89 years (mean age of 73) with either: a femoral neck BMD T-score less than or equal to -1.5 and at least two mild or one moderate existing vertebral fracture(s); or a femoral neck BMD T-score less than or equal to -2.5 with or without evidence of an existing vertebral fracture(s). Women were stratified into two groups: Stratum I: no concomitant use of osteoporosis therapy or Stratum II: baseline concomitant use of osteoporosis therapies, which included calcitonin, raloxifene, tamoxifen, and hormone replacement therapy, but excluded other bisphosphonates.

Women enrolled in Stratum I (n=5661) were evaluated annually for incidence of vertebral fractures. All women (Strata I and II) were evaluated for the incidence of hip and other clinical fractures. Reclast was administered once a year for three consecutive years, as a single 5 mg dose in 100 mL solution infused over at least 15 minutes, for a total of three doses. All women received 1000 to 1500 mg of elemental calcium plus 400 to 1200 international units of vitamin D supplementation per day.

The two primary efficacy variables were the incidence of morphometric vertebral fractures at 3 years and the incidence of hip fractures over a median duration of 3 years. The diagnosis of an incident vertebral fracture was based on both qualitative diagnosis by the radiologist and quantitative morphometric criterion. The morphometric criterion required the dual occurrence of 2 events: a relative height ratio or relative height reduction in a vertebral body of at least 20%, together with at least a 4 mm absolute decrease in height.

Effect on Vertebral Fractures

Reclast significantly decreased the incidence of new vertebral fractures at one, two, and three years as shown in Table 5.

Table 5. Proportion of Patients with New Morphometric Vertebral Fractures
Outcome | Reclast (%) | Placebo (%) | Absolute Reduction in Fracture Incidence % (95% CI) | Relative Reduction in Fracture Incidence % (95% CI)
At least one new vertebral fracture (0 to 1 year) | 1.5 | 3.7 | 2.2 (1.4, 3.1) | 60 (43, 72) [p < 0.0001]
At least one new vertebral fracture (0 to 2 years) | 2.2 | 7.7 | 5.5 (4.4, 6.6) | 71 (62, 78)
At least one new vertebral fracture (0 to 3 years) | 3.3 | 10.9 | 7.6 (6.3, 9.0) | 70 (62, 76)

The reductions in vertebral fractures over three years were consistent (including new/worsening and multiple vertebral fractures) and significantly greater than placebo regardless of age, geographical region, baseline body mass index, number of baseline vertebral fractures, femoral neck BMD T-score, or prior bisphosphonate usage.

Effect on Hip Fracture Over 3 years

Reclast demonstrated a 1.1% absolute reduction and 41% relative reduction in the risk of hip fractures over a median duration of follow-up of 3 years. The hip fracture event rate was 1.4% for Reclast-treated patients compared to 2.5% for placebo-treated patients.

Figure 1. Cumulative Incidence of Hip Fracture Over 3 Years

The reductions in hip fractures over three years were greater for Reclast than placebo regardless of femoral neck BMD T-score.

Effect on All Clinical Fractures

Reclast demonstrated superiority to placebo in reducing the incidence of all clinical fractures, clinical (symptomatic) vertebral and non-vertebral fractures (excluding finger, toe, facial, and clinical thoracic and lumbar vertebral fractures). All clinical fractures were verified based on the radiographic and/or clinical evidence. A summary of results is presented in Table 6.

Table 6. Between-Treatment Comparisons of the Incidence of Clinical Fracture Variables Over 3 Years
Outcome | Reclast (N = 3875) Event Rate n (%) [Event rates based on Kaplan-Meier estimates at 36 months] | Placebo (N = 3861) Event Rate n (%) | Absolute Reduction in Fracture Incidence % (95% CI) | Relative Risk Reduction in Fracture Incidence % (95% CI)
Any clinical fracture [Excluding finger, toe, and facial fractures.] | 308 (8.4) | 456 (12.8) | 4.4 (3.0, 5.8) | 33 (23, 42)**
Clinical vertebral fracture [Includes clinical thoracic and clinical lumbar vertebral fractures.] | 19 (0.5) | 84 (2.6) | 2.1 (1.5, 2.7) | 77 (63, 86)**
Non-vertebral fracture [Excluding finger, toe, facial, and clinical thoracic and lumbar vertebral fractures.] | 292 (8.0) | 388 (10.7) | 2.7 (1.4, 4.0) | 25 (13, 36) [p-value < 0.001, **p-value < 0.0001.]

Effect on Bone Mineral Density

Reclast significantly increased BMD at the lumbar spine, total hip and femoral neck, relative to treatment with placebo at time points 12, 24, and 36 months. Treatment with Reclast resulted in a 6.7% increase in BMD at the lumbar spine, 6.0% at the total hip, and 5.1% at the femoral neck, over 3 years as compared to placebo.

Bone Histology

Bone biopsy specimens were obtained between Months 33 and 36 from 82 postmenopausal patients with osteoporosis treated with 3 annual doses of Reclast. Of the biopsies obtained, 81 were adequate for qualitative histomorphometry assessment, 59 were adequate for partial quantitative histomorphometry assessment, and 38 were adequate for full quantitative histomorphometry assessment. Micro CT analysis was performed on 76 specimens. Qualitative, quantitative and micro CT assessments showed bone of normal architecture and quality without mineralization defects.

Effect on Height

In the 3-year osteoporosis study, standing height was measured annually using a stadiometer. The Reclast group revealed less height loss compared to placebo (4.2 mm vs. 7.0 mm, respectively [p < 0.001]).

Study 2: The efficacy and safety of Reclast in the treatment of patients with osteoporosis who suffered a recent low-trauma hip fracture was demonstrated in Study 2, a randomized, double-blind, placebo-controlled, multinational endpoint study of 2127 men and women aged 50 to 95 years (mean age of 74.5). Concomitant osteoporosis therapies excluding other bisphosphonates and parathyroid hormone were allowed. Reclast was administered once a year as a single 5 mg dose in 100 mL solution, infused over at least 15 minutes. The study continued until at least 211 patients had confirmed clinical fractures in the study population. Vitamin D levels were not routinely measured but a loading dose of vitamin D (50,000 to 125,000 international units orally or IM) was given to patients and they were started on 1000 to 1500 mg of elemental calcium plus 800 to 1200 international units of vitamin D supplementation per day for at least 14 days prior to the study drug infusions. The primary efficacy variable was the incidence of clinical fractures over the duration of the study.

Reclast significantly reduced the incidence of any clinical fracture by 35%. There was also a 46% reduction in the risk of a clinical vertebral fracture (Table 7).

Table 7. Between-Treatment Comparisons of the Incidence of Key Clinical Fracture Variables
Outcome | Reclast (N = 1065) Event Rate n (%) [Event rates based on Kaplan-Meier estimates at 24 months.] | Placebo (N = 1062) Event Rate n (%) | Absolute Reduction in Fracture Incidence % (95% CI) | Relative Risk Reduction in Fracture Incidence % (95% CI)
Any clinical fracture [Excluding finger, toe and facial fractures.] | 92 (8.6) | 139 (13.9) | 5.3 (2.3, 8.3) | 35 (16, 50)**
Clinical vertebral fracture [Including clinical thoracic and clinical lumbar vertebral fractures.] | 21 (1.7) | 39 (3.8) | 2.1 (0.5, 3.7) | 46 (8, 68) [p-value < 0.05, **p-value < 0.005.]

Effect on Bone Mineral Density

Reclast significantly increased BMD relative to placebo at the hip and femoral neck at all timepoints (12, 24, and 36 months). Treatment with Reclast resulted in a 6.4% increase in BMD at the total hip and a 4.3% increase at the femoral neck over 36 months as compared to placebo.

14.2 Prevention of Postmenopausal Osteoporosis

The efficacy and safety of Reclast in postmenopausal women with osteopenia (low bone mass) was assessed in a 2-year randomized, multi-center, double-blind, placebo-controlled study of 581 postmenopausal women aged greater than or equal to 45 years, who were stratified by years since menopause: Stratum I women less than 5 years from menopause (n=224); Stratum II women greater than or equal to 5 years from menopause (n=357). Patients within Stratum I and II were randomized to one of three treatment groups: (1) Reclast given at randomization and at Month 12 (n=77) in Stratum I and (n=121) in Stratum II; (2) Reclast given at randomization and placebo at Month 12 (n=70) in Stratum I and (n=111) in Stratum II; and (3) Placebo given at randomization and Month 12 (n=202). Reclast was administered as a single 5 mg dose in 100 mL solution infused over at least 15 minutes. All women received 500 to 1200 mg elemental calcium plus 400 to 800 international units vitamin D supplementation per day. The primary efficacy variable was the percent change of BMD at 24 Months relative to baseline.

Effect on Bone Mineral Density

Reclast significantly increased lumbar spine BMD relative to placebo at Month 24 across both strata. Reclast given once at randomization (and placebo given at Month 12) resulted in 4.0% increase in BMD in Stratum I patients and 4.8% increase in Stratum II patients over 24 months. Placebo given at randomization and at Month 12 resulted in 2.2% decrease in BMD in Stratum I patients and 0.7% decrease in BMD in Stratum II patients over 24 months. Therefore, Reclast given once at randomization (and placebo given at Month 12) resulted in a 6.3% increase in BMD in Stratum I patients and 5.4% increase in Stratum II patients over 24 months as compared to placebo (both p < 0.0001).

Reclast also significantly increased total hip BMD relative to placebo at Month 24 across both strata. Reclast given once at randomization (and placebo given at Month 12) resulted in 2.6% increase in BMD in Stratum I patients and 2.1% in Stratum II patients over 24 months. Placebo given at randomization and at Month 12 resulted in 2.1% decrease in BMD in Stratum I patients and 1.0% decrease in BMD in Stratum II patients over 24 months. Therefore, Reclast given once at randomization (and placebo given at Month 12) resulted in a 4.7% increase in BMD in Stratum I patients and 3.2% increase in Stratum II patients over 24 months as compared to placebo (both p < 0.0001).

14.3 Osteoporosis in Men

The efficacy and safety of Reclast in men with osteoporosis or significant osteoporosis secondary to hypogonadism, was assessed in a randomized, multicenter, double-blind, active controlled, study of 302 men aged 25 to 86 years (mean age of 64). The duration of the trial was two years. Patients were randomized to either Reclast, which was administered once annually as a 5 mg dose in 100 mL infused over 15 minutes for a total of up to two doses, or to an oral weekly bisphosphonate (active control) for up to two years. All participants received 1000 mg of elemental calcium plus 800 to 1000 international units of vitamin D supplementation per day.

Effect on Bone Mineral Density

An annual infusion of Reclast was non-inferior to the oral weekly bisphosphonate active control based on the percentage change in lumbar spine BMD at Month 24 relative to baseline (Reclast: 6.1% increase; active control: 6.2% increase).

14.4 Treatment and Prevention of Glucocorticoid-Induced Osteoporosis

The efficacy and safety of Reclast to prevent and treat glucocorticoid-induced osteoporosis (GIO) was assessed in a randomized, multicenter, double-blind, stratified, active controlled study of 833 men and women aged 18 to 85 years (mean age of 54.4 years) treated with greater than or equal to 7.5 mg/day oral prednisone (or equivalent). Patients were stratified according to the duration of their pre-study corticosteroid therapy: less than or equal to 3 months prior to randomization (prevention subpopulation), and greater than 3 months prior to randomization (treatment subpopulation). The duration of the trial was one year. Patients were randomized to either Reclast, which was administered once as a 5 mg dose in 100 mL infused over 15 minutes, or to an oral daily bisphosphonate (active control) for one year. All participants received 1000 mg of elemental calcium plus 400 to 1000 international units of vitamin D supplementation per day.

Effect on Bone Mineral Density

In the GIO treatment subpopulation, Reclast demonstrated a significant mean increase in lumbar spine BMD compared to the active control at one year (Reclast 4.1%, active control 2.7%) with a treatment difference of 1.4% (p < 0.001). In the GIO prevention subpopulation, Reclast demonstrated a significant mean increase in lumbar spine BMD compared to active control at one year (Reclast 2.6%, active control 0.6%) with a treatment difference of 2.0% (p < 0.001).

Bone Histology

Bone biopsy specimens were obtained from 23 patients (12 in the Reclast treatment group and 11 in the active control treatment group) at Month 12 treated with an annual dose of Reclast or daily oral active control. Qualitative assessments showed bone of normal architecture and quality without mineralization defects. Apparent reductions in activation frequency and remodeling rates were seen when compared with the histomorphometry results seen with Reclast in the postmenopausal osteoporosis population. The long-term consequences of this degree of suppression of bone remodeling in glucocorticoid-treated patients is unknown.

14.5 Treatment of Paget’s Disease of Bone

Reclast was studied in male and female patients with moderate to severe Paget’s disease of bone, defined as serum alkaline phosphatase level at least twice the upper limit of the age-specific normal reference range at the time of study entry. Diagnosis was confirmed by radiographic evidence.

The efficacy of one infusion of 5 mg Reclast vs. oral daily doses of 30 mg risedronate for 2 months was demonstrated in two identically designed 6-month randomized, double-blind trials. The mean age of patients in the two trials was 70. Ninety-three percent (93%) of patients were Caucasian. Therapeutic response was defined as either normalization of serum alkaline phosphatase (SAP) or a reduction of at least 75% from baseline in total SAP excess at the end of 6 months. SAP excess was defined as the difference between the measured level and midpoint of normal range.

In both trials, Reclast demonstrated a superior and more rapid therapeutic response compared with risedronate and returned more patients to normal levels of bone turnover, as evidenced by biochemical markers of formation (SAP, serum N-terminal propeptide of type I collagen [P1NP]) and resorption (serum CTx 1 [cross-linked C-telopeptides of type I collagen] and urine α-CTx).

The 6-month combined data from both trials showed that 96% (169/176) of Reclast-treated patients achieved a therapeutic response as compared with 74% (127/171) of patients treated with risedronate. Most Reclast patients achieved a therapeutic response by the Day 63 visit. In addition, at 6 months, 89% (156/176) of Reclast-treated patients achieved normalization of SAP levels, compared to 58% (99/171) of patients treated with risedronate (p < 0.0001) (see Figure 2).

Figure 2. Therapeutic Response/Serum Alkaline Phosphatase (SAP) Normalization Over Time

The therapeutic response to Reclast was similar across demographic and disease-severity groups defined by gender, age, previous bisphosphonate use, and disease severity. At 6 months, the percentage of Reclast-treated patients who achieved therapeutic response was 97% and 95%, respectively, in each of the baseline disease severity subgroups (baseline SAP less than 3xULN, greater than or equal to 3xULN) compared to 75% and 74%, respectively, for the same disease severity subgroups of risedronate-treated patients.

In patients who had previously received treatment with oral bisphosphonates, therapeutic response rates were 96% and 55% for Reclast and risedronate, respectively. The comparatively low risedronate response was due to the low response rate (7/23, 30%) in patients previously treated with risedronate. In patients naïve to previous treatment, a greater therapeutic response was also observed with Reclast (98%) relative to risedronate (86%). In patients with symptomatic pain at screening, therapeutic response rates were 94% and 70% for Reclast and risedronate, respectively. For patients without pain at screening, therapeutic response rates were 100% and 82% for Reclast and risedronate, respectively.

Bone histology was evaluated in 7 patients with Paget’s disease 6 months after being treated with Reclast 5 mg. Bone biopsy results showed bone of normal quality with no evidence of impaired bone remodeling and no evidence of mineralization defect.

16 HOW SUPPLIED/STORAGE AND HANDLING

Each bottle contains 5 mg per 100 mL NDC 66758-155-46

Handling

After opening the solution, it is stable for 24 hours at 2°C to 8°C (36°F to 46°F).

If refrigerated, allow the refrigerated solution to reach room temperature before administration.

Storage

Store at 20°C to 25°C (68°F to 77°F); excursions permitted between 15°C and 30°C (59°F to 86°F) [see USP Controlled Room Temperature].

17 PATIENT COUNSELING INFORMATION

Advise the patient to read the FDA-approved patient labeling (Medication Guide).

Information for Patients

Patients should be made aware that Reclast contains the same active ingredient (zoledronic acid) found in Zometa®, and that patients being treated with Zometa should not be treated with Reclast.

Reclast is contraindicated in patients with creatinine clearance less than 35 mL/min [see Contraindications (4)].

Before being given Reclast, patients should tell their doctor if they have kidney problems and what medications they are taking [see Warnings and Precautions (5.3)].

Reclast should not be given if the patient is pregnant or plans to become pregnant, or if she is breastfeeding [see Use in Specific Populations (8.1, 8.2, 8.3)].

There have been reports of bronchoconstriction in aspirin-sensitive patients receiving bisphosphonates, including Reclast. Before being given Reclast, patients should tell their doctor if they are aspirin-sensitive.

If the patient had surgery to remove some or all of the parathyroid glands in their neck, or had sections of their intestine removed, or are unable to take calcium supplements they should tell their doctor.

Reclast is given as an infusion into a vein by a nurse or a doctor, and the infusion time must not be less than 15 minutes.

On the day of treatment the patient should eat and drink normally, which includes drinking at least 2 glasses of fluid, such as water within a few hours prior to the infusion, as directed by their doctor, before receiving Reclast.

After getting Reclast it is strongly recommended patients with Paget’s disease take calcium in divided doses (for example, 2 to 4 times a day) for a total of 1500 mg calcium a day to prevent low blood calcium levels. This is especially important for the two weeks after getting Reclast [see Warnings and Precautions (5.2)].

Adequate calcium and vitamin D intake is important in patients with osteoporosis and the current recommended daily intake of calcium is 1200 mg and vitamin D is 800 international units to 1000 international units daily. All patients should be instructed on the importance of calcium and vitamin D supplementation in maintaining serum calcium levels.

Patients should be aware of the most commonly associated side effects of therapy. Patients may experience one or more side effects that could include: fever, flu-like symptoms, myalgia, arthralgia, and headache. Most of these side effects occur within the first 3 days following the dose of Reclast. They usually resolve within 3 days of onset but may last for up to 7 to 14 days. Patients should consult their physician if they have questions or if these symptoms persist. The incidence of these symptoms decreased markedly with subsequent doses of Reclast.

Administration of acetaminophen following Reclast administration may reduce the incidence of these symptoms.

Physicians should inform their patients that there have been reports of persistent pain and/or a non-healing sore of the mouth or jaw, primarily in patients treated with bisphosphonates for other illnesses. During treatment with zoledronic acid, patients should be instructed to maintain good oral hygiene and undergo routine dental check-ups. If they experience any oral symptoms, they should immediately report them to their physician or dentist.

Severe and occasionally incapacitating bone, joint, and/or muscle pain have been infrequently reported in patients taking bisphosphonates, including Reclast. Consider withholding future Reclast treatment if severe symptoms develop.

Atypical femur fractures in patients on bisphosphonate therapy have been reported; patients with thigh or groin pain should be evaluated to rule out a femoral fracture.

MEDICATION GUIDE
Reclast® (RE-clast)
(zoledronic acid)
Injection

Read the Medication Guide that comes with Reclast before you start taking it and each time you get a refill. There may be new information. This Medication Guide does not take the place of talking with your doctor about your medical condition or treatment. Talk to your doctor if you have any questions about Reclast.

What is the most important information I should know about Reclast?
You should not receive Reclast if you are already receiving Zometa. Both Reclast and Zometa contain zoledronic acid.
Reclast can cause serious side effects, including:

1. Low calcium levels in your blood (hypocalcemia)
2. Severe kidney problems
3. Severe jaw bone problems (osteonecrosis)
4. Unusual breaks in thigh and other bones
5. Bone, joint or muscle pain

1. Low calcium levels in your blood (hypocalcemia).

Reclast may lower the calcium levels in your blood. If you have low blood calcium before you start taking Reclast, it may get worse during treatment. Your low blood calcium must be treated before you take Reclast. Most people with low blood calcium levels do not have symptoms, but some people may have symptoms. Call your doctor right away if you have symptoms of low blood calcium, such as:

- Spasms, twitches, or cramps in your muscles
- Numbness or tingling in your fingers, toes, or around your mouth

Your doctor may prescribe calcium and vitamin D to help prevent low calcium levels in your blood, while you take Reclast. Take calcium and vitamin D as your doctor tells you to.

2. Severe kidney problems.

Severe kidney problems may happen when you take Reclast. Severe kidney problems may lead to hospitalization or kidney dialysis and can be life-threatening. Your risk of kidney problems is higher if you:

- already have kidney problems
- take a diuretic or “water pill”
- do not have enough water in your body (dehydrated) before or after you receive Reclast
- are of advanced age since the risk increases as you get older
- take any medicines known to harm your kidneys

You should drink at least 2 glasses of fluid within a few hours before receiving Reclast to reduce the risk of kidney problems.

3. Severe jaw bone problems (osteonecrosis).

Severe jaw bone problems may happen when you take Reclast. Your doctor should examine your mouth before you start Reclast. Your doctor may tell you to see your dentist before you start Reclast. It is important for you to practice good mouth care during treatment with Reclast.

4. Unusual breaks in thigh and other bones.

Some people have had unusual bone breaks, including thigh bone, when taking Reclast. A break in the thigh bone can feel like a new pain in your hip, groin, or thigh. People taking Reclast can also have breaks in other bones.

5. Bone, joint, or muscle pain.

Some people who take bisphosphonates develop severe bone, joint, or muscle pain.

Call your doctor right away if you have any of these side effects.

What is Reclast?
Reclast is a prescription medicine used to:

- Treat or prevent osteoporosis in women after menopause. Reclast helps reduce the chance of having a hip or spinal fracture (break).
- Increase bone mass in men with osteoporosis.
- Treat or prevent osteoporosis in either men or women who will be taking corticosteroid medicines for at least one year.
- Treat certain men and women who have Paget’s disease of the bone.

It is not known how long Reclast works for the treatment and prevention of osteoporosis. You should see your doctor regularly to determine if Reclast is still right for you.
Reclast is not for use in children.

Who should not take Reclast?
Do not take Reclast if you:

- Have low levels of calcium in your blood.
- Have kidney problems.
- Are allergic to zoledronic acid or any of its ingredients. A list of ingredients is at the end of this leaflet.

What should I tell my doctor before taking Reclast?
Before you start Reclast, be sure to talk to your doctor if you:

- Have low blood calcium.
- Have kidney problems.
- Had parathyroid or thyroid surgery (glands in your neck).
- Have been told you have trouble absorbing minerals in your stomach or intestines (malabsorption syndrome) or have had parts of your intestine removed
- Have asthma (wheezing) from taking aspirin.
- Plan to have dental surgery or teeth removed.
- Are pregnant, or plan to become pregnant. Reclast should not be used if you are pregnant. It is not known if Reclast can harm your unborn baby.
- Are breastfeeding or plan to breastfeed. It is not known if Reclast passes into your milk and may harm your baby. Tell your doctor about all the medicines you take, including prescription and non-prescription medicines, vitamins, and herbal supplements. Certain medicines may affect how Reclast works.

Especially tell your doctor if you are taking:

- An antibiotic. Certain antibiotic medicines called aminoglycosides may increase the effect of Reclast in lowering your blood calcium for a long period of time.
- A diuretic or “water pill”.
- Non-steroidal anti-inflammatory medicines (NSAIDS).

Ask your doctor or pharmacist for a list of these medicines, if you are not sure.
Know the medicines you take. Keep a list of them and show it to your doctor and pharmacist each time you get a new medicine.

How will I receive Reclast?

- Your doctor will tell you how often you will receive Reclast.
- Reclast is given by infusion into your vein (intravenously). Your infusion should last at least 15 minutes.
- Before you receive Reclast, drink at least 2 glasses of fluid (such as water) within a few hours as directed by your doctor.
- You may eat before your treatment with Reclast.
- If you miss a dose of Reclast, call your doctor or healthcare provider to schedule your next dose.

What are the possible side effects of Reclast?
Reclast may cause serious side effects.

- See “What is the most important information I should know about Reclast?”

The most common side effects of Reclast included:

- Fever
- Pain in your bones, joints or muscles
- Pain in your arms and legs
- Headache
- Flu-like illness (fever, chills, bone, joint, or muscle pain, fatigue)
- Nausea
- Vomiting
- Diarrhea

Talk to your doctor about things you can do to help decrease some of these side effects that might happen with a Reclast infusion.

You may get allergic reactions, such as hives, swelling of your face, lips, tongue, or throat.
Tell your doctor if you have any side effect that bothers you or that does not go away.
These are not all the possible side effects of Reclast. For more information, ask your doctor or pharmacist.

Call your doctor for medical advice about side effects. You may report side effects to FDA at 1-800-FDA-1088.

General information about safe and effective use of Reclast.
Medicines are sometimes prescribed for purposes other than those listed in a Medication Guide.
This Medication Guide summarizes the most important information about Reclast. If you would like more information, talk with your doctor. You can ask your doctor or pharmacist for information about Reclast that is written for health professionals.
For more information go to www.sandoz.com or call 1-800-525-8747.

What are the ingredients in Reclast?
Active ingredient: zoledronic acid monohydrate.
Inactive ingredients: mannitol and sodium citrate.
Manufactured by:

Fresenius Kabi Austria GmbH

Graz, Austria for

Sandoz Inc., Princeton, NJ 08540

24.0199.005.5600121 US

This Medication Guide has been approved by the U.S. Food and Drug Administration. Revised: February/2026

PRINCIPAL DISPLAY PANEL

NDC 66758-155-46

Rx only

Reclast®

(zoledronic acid) injection

5 mg/100 mL

Solution for Intravenous Infusion

Dispense the accompanying Medication Guide to each patient.

1 bottle – Sterile Solution

Do not mix with calcium-containing solutions. Administer as a single intravenous
solution through a separate vented infusion line.

SANDOZ